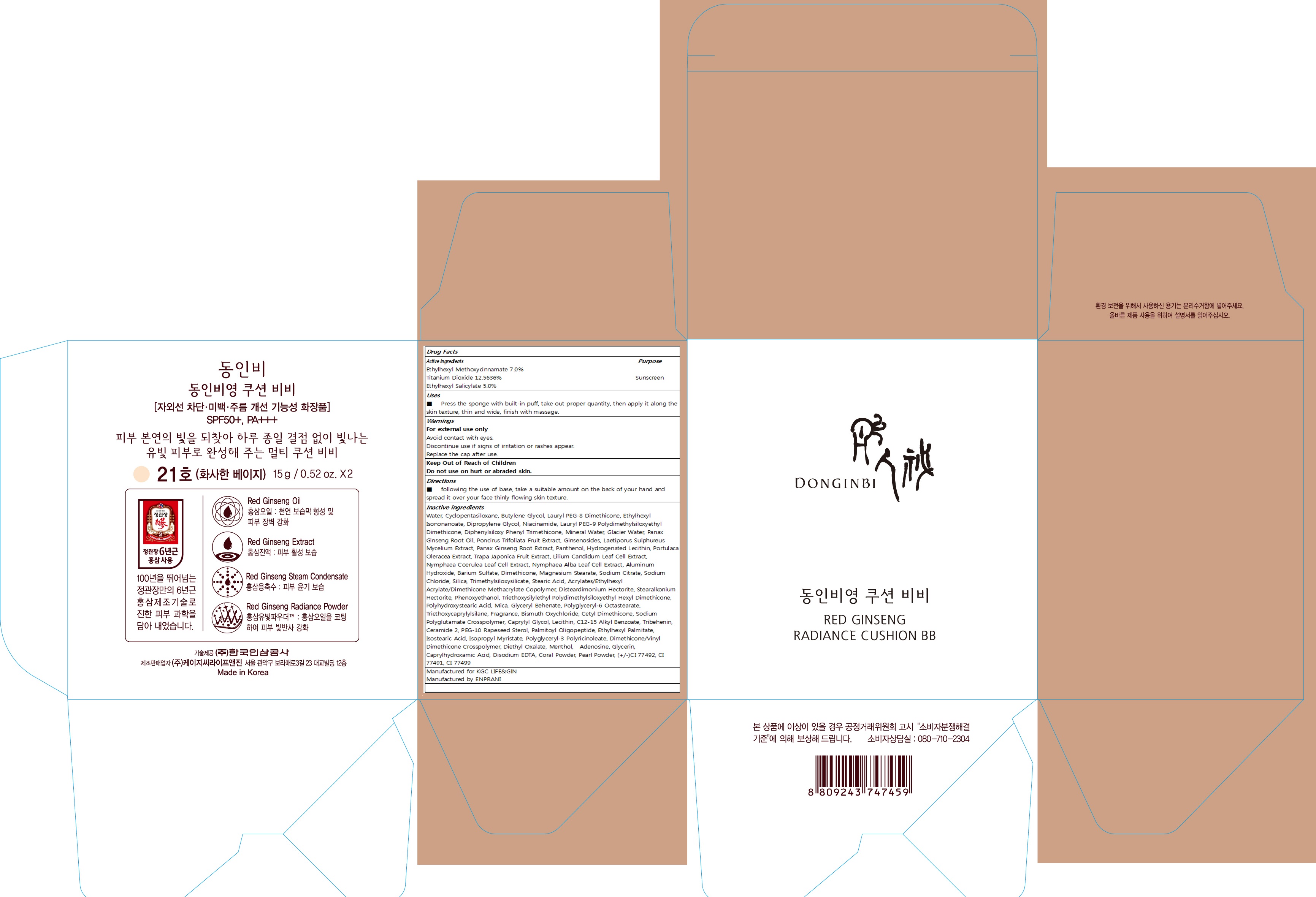 DRUG LABEL: DONGINBI RED GINSENG RADIANCE
NDC: 69640-5001 | Form: POWDER
Manufacturer: KGC LIFE&GIN
Category: otc | Type: HUMAN OTC DRUG LABEL
Date: 20170726

ACTIVE INGREDIENTS: Octinoxate 1.05 g/15 g; Octisalate 0.75 g/15 g; Titanium Dioxide 1.88 g/15 g
INACTIVE INGREDIENTS: Water; Butylene Glycol

ACTIVE INGREDIENT

Active ingredients: Ethylhexyl Methoxycinnamate 7.0%, Titanium Dioxide 12.5636%, Ethylhexyl Salicylate 5.0%

INACTIVE INGREDIENT

Inactive ingredients: Water, Cyclopentasiloxane, Butylene Glycol, Lauryl PEG-8 Dimethicone, Ethylhexyl Isononanoate, Dipropylene Glycol, Niacinamide, Lauryl PEG-9 Polydimethylsiloxyethyl Dimethicone, Diphenylsiloxy Phenyl Trimethicone, Mineral Water, Glacier Water, Panax Ginseng Root Oil, Poncirus Trifoliata Fruit Extract, Ginsenosides, Laetiporus Sulphureus Mycelium Extract, Panax Ginseng Root Extract, Panthenol, Hydrogenated Lecithin, Portulaca Oleracea Extract, Trapa Japonica Fruit Extract, Lilium Candidum Leaf Cell Extract, Nymphaea Coerulea Leaf Cell Extract, Nymphaea Alba Leaf Cell Extract, Aluminum Hydroxide, Barium Sulfate, Dimethicone, Magnesium Stearate, Sodium Citrate, Sodium Chloride, Silica, Trimethylsiloxysilicate, Stearic Acid, Acrylates/Ethylhexyl Acrylate/Dimethicone Methacrylate Copolymer, Disteardimonium Hectorite, Stearalkonium Hectorite, Phenoxyethanol, Triethoxysilylethyl Polydimethylsiloxyethyl Hexyl Dimethicone, Polyhydroxystearic Acid, Mica, Glyceryl Behenate, Polyglyceryl-6 Octastearate, Triethoxycaprylylsilane, Fragrance, Bismuth Oxychloride, Cetyl Dimethicone, Sodium Polyglutamate Crosspolymer, Caprylyl Glycol, Lecithin, C12-15 Alkyl Benzoate, Tribehenin, Ceramide 2, PEG-10 Rapeseed Sterol, Palmitoyl Oligopeptide, Ethylhexyl Palmitate, Isostearic Acid, Isopropyl Myristate, Polyglyceryl-3 Polyricinoleate, Dimethicone/Vinyl Dimethicone Crosspolymer, Diethyl Oxalate, Menthol, Adenosine, Glycerin, Caprylhydroxamic Acid, Disodium EDTA, Coral Powder, Pearl Powder, (+/-)CI 77492, CI 77491, CI 77499

PURPOSE

Purpose: Sunscreen

WARNINGS

Warnings: For external use only. Avoid contact with eyes. Discontinue use if signs of irritation or rashes appear. Replace the cap after use.

Keep Out of Reach of Children: Do not use on hurt or abraded skin.

DESCRIPTION

Uses: Press the sponge with built-in puff, take out proper quantity, then apply it along the skin texture, thin and wide, finish with massage.

Directions: following the use of base, take a suitable amount on the back of your hand and spread it over your face thinly flowing skin texture.